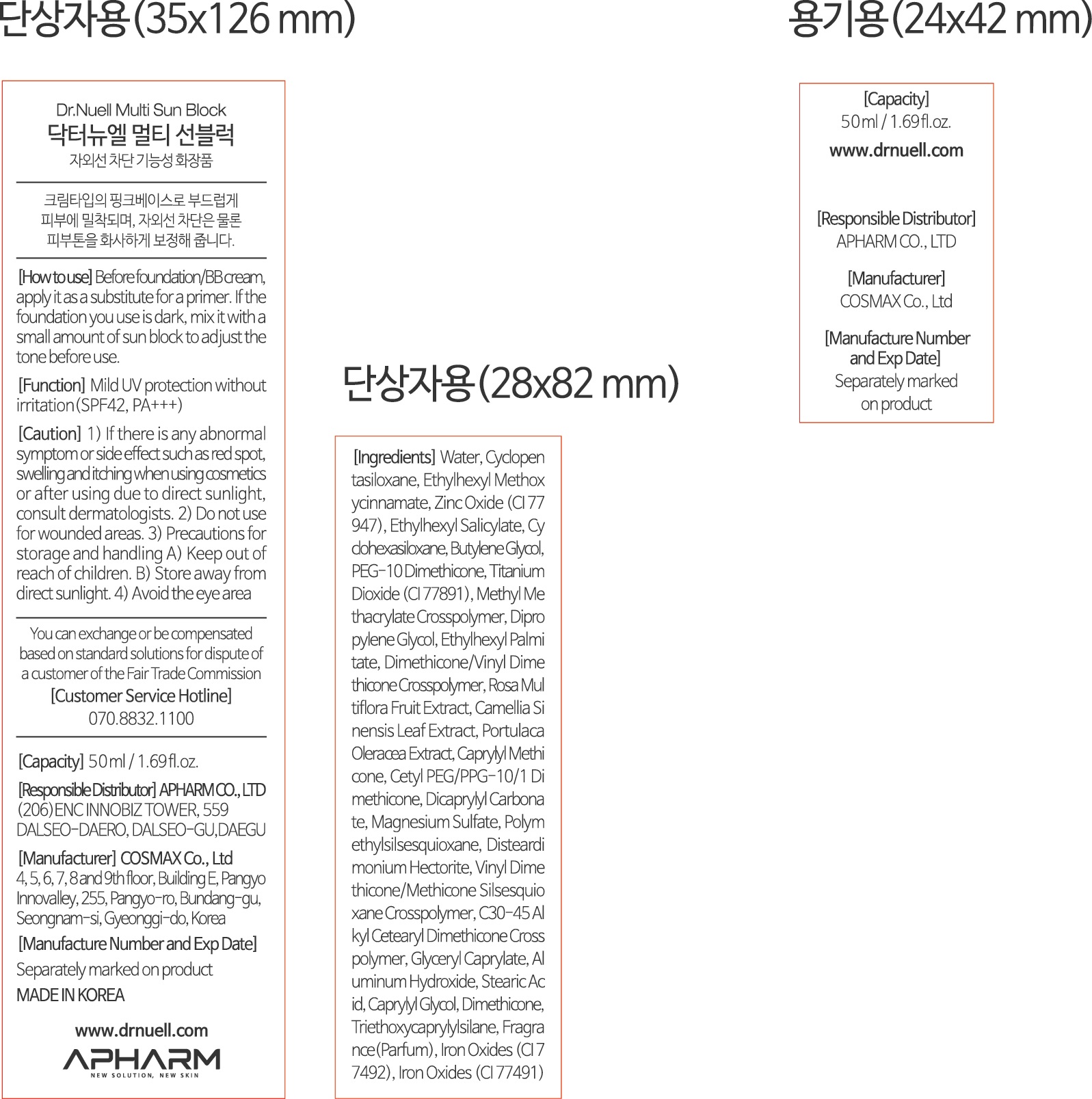 DRUG LABEL: Dr.NUELL Multi Sun Block
NDC: 73430-0005 | Form: CREAM
Manufacturer: Apharm Co., Ltd.
Category: otc | Type: HUMAN OTC DRUG LABEL
Date: 20191103

ACTIVE INGREDIENTS: ZINC OXIDE 4.9004028 g/100 mL
INACTIVE INGREDIENTS: WATER; BUTYLENE GLYCOL

ACTIVE INGREDIENT

zinc oxide

Keep out of reach of children

INDICATIONS AND USAGE

before foundation BB cream, apply it as a substitute for a primer.

if the foundation you use is dark, mix it with a small amount of sun block to adjust the tone before use

WARNINGS

1) if there is any abnormal symptom or side effect, such as red spot, swelling and itching when using cosmetlcs or after using due to direct sunlight, consult dermatologists
2) Do not use for wounded areas
3) Precautions for storage and handling
keep out of reach of children, store away from direct sunlight
4) avoid the eye area

INACTIVE INGREDIENT

water, butylene glycol, cyclopentasiloxane, etc.

DOSAGE AND ADMINISTRATION

For external use only

PURPOSE

dual functionality for brightening and wrinkle improvement certified

PURPOSE

mild UV protection without irritation SPF 42, PA+++